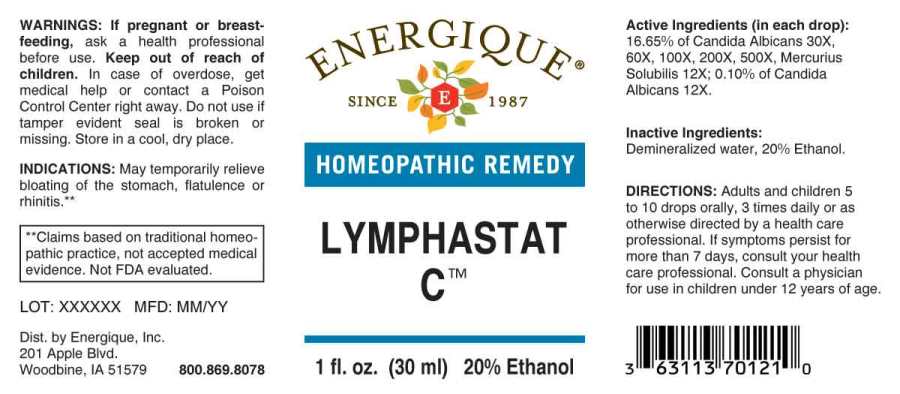 DRUG LABEL: Lymphastat C
NDC: 44911-0603 | Form: LIQUID
Manufacturer: Energique, Inc.
Category: homeopathic | Type: HUMAN OTC DRUG LABEL
Date: 20240513

ACTIVE INGREDIENTS: MERCURIUS SOLUBILIS 12 [hp_X]/1 mL; CANDIDA ALBICANS 12 [hp_X]/1 mL
INACTIVE INGREDIENTS: WATER; ALCOHOL

Drug Facts:

ACTIVE INGREDIENTS:

(in each drop): 16.65% of Candida Albicans 30X, 60X, 100X, 200X, 500X, Mercurius Solubilis 12X; 0.10% of Candida Albicans 12X.

INDICATIONS:

For temporary relief of bloating of the stomach, flatulence or rhinitis.**

**Claims based on traditional homeopathic practice, not accepted medical evidence. Not FDA evaluated.

WARNINGS:

If pregnant or breast-feeding, ask a health professional before use.

Keep out of reach of children. In case of overdose, get medical help or contact a Poison Control Center right away.

Do not use if tamper evident seal is broken or missing. Store in a cool, dry place.

Keep out of reach of children. In case of overdose, get medical help or contact a Poison Control Center right away.

DIRECTIONS:

Adults and children 5 to 10 drops orally, 3 times daily or as otherwise directed by a health care professional. If symptoms persist, consult your health care professional.

Consult a physician for use in children under 12 years of age.

INDICATIONS:

For temporary relief of bloating of the stomach, flatulence or rhinitis.**

**Claims based on traditional homeopathic practice, not accepted medical evidence. Not FDA evaluated.

INACTIVE INGREDIENTS:

Demineralized water, 20% Ethanol

QUESTIONS:

Dist. by Energique, Inc.

201 Apple Blvd

Woodbine, IA 51579 800-869-8078

PACKAGE LABEL DISPLAY:

ENERGIQUE

SINCE 1987

HOMEOPATHIC REMEDY

LYMPHASTAT C

1 fl. oz. (30 ml)